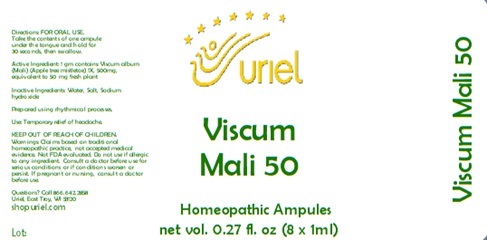 DRUG LABEL: Viscum Mali 50
NDC: 48951-9313 | Form: LIQUID
Manufacturer: Uriel Pharmacy Inc.
Category: homeopathic | Type: HUMAN OTC DRUG LABEL
Date: 20241119

ACTIVE INGREDIENTS: VISCUM ALBUM FRUITING TOP 1 [hp_X]/1 mL
INACTIVE INGREDIENTS: WATER; SODIUM CHLORIDE; SODIUM HYDROXIDE

Viscum Mali 50

INDICATIONS AND USAGE

Directions: FOR ORAL USE.

DOSAGE AND ADMINISTRATION

Take the contents of one ampule under the tongue and hold for 30 seconds, then swallow.

Inactive Ingredients: Water, Salt, Sodium hydroxide

Prepared using rhythmical processes.

Active Ingredient: 1 gm contains: Viscum album (Mali) (Apple tree mistletoe) 1X, 500mg, equivalent to 50 mg fresh plant

PURPOSE

Use: Temporary relief of headache.

KEEP OUT OF REACH OF CHILDREN.

WARNINGS

Warnings: Claims based on traditional homeopathic practice, not accepted medical evidence. Not FDA evaluated. Do not use if allergic to any ingredient. Consult a doctor before use for serious conditions or if conditions worsen or persist. If pregnant or nursing, consult a doctor before use.

Questions? Call 866.642.2858
Uriel, East Troy, WI 53120
shopuriel.com Lot: